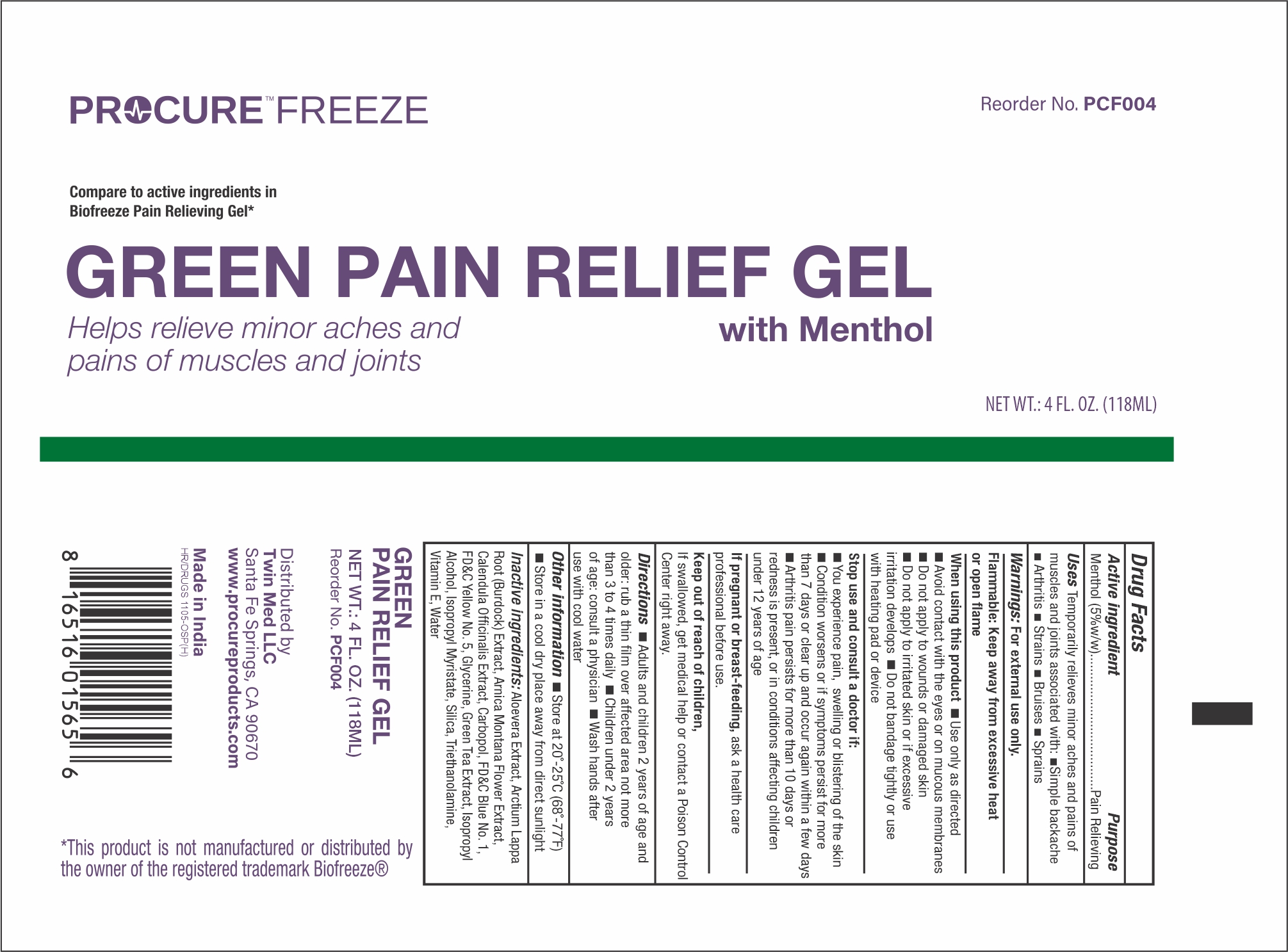 DRUG LABEL: Procure gel
NDC: 55681-015 | Form: GEL
Manufacturer: TWIN MED, LLC
Category: otc | Type: HUMAN OTC DRUG LABEL
Date: 20250620

ACTIVE INGREDIENTS: MENTHOL 5 g/100 g
INACTIVE INGREDIENTS: FD&C BLUE NO. 1; SILICON DIOXIDE; FD&C YELLOW NO. 5; ALOE VERA LEAF; ARCTIUM LAPPA ROOT; ARNICA MONTANA FLOWER; CALENDULA OFFICINALIS FLOWER; GREEN TEA LEAF; CARBOXYPOLYMETHYLENE; GLYCERIN; ISOPROPYL ALCOHOL; ISOPROPYL MYRISTATE; .ALPHA.-TOCOPHEROL; TROLAMINE; WATER

PROCURE GREEN PAIN GEL

Active Ingredients

Menthol 5%

Purpose

Pain Relieving

Uses

Temporarily relieves minor aches and pains of muscles and joints associated with: ■Simple backache

Arthritis ■Strains ■Bruises ■Sprains

Warnings

For external use only

Flammable:

Keep away from excessive heat or open flame.

When using this product:

■Use only as directed

■Avoid contact with the eyes or on mucous membranes

■Do not apply to wounds or damaged skin

■Do not apply to irritated skin or if excessive irritation develops ■Do not bandage tightly or use with heating pad or device

Stop use and ask a doctor if:

■You experience pain, swelling or blistering of the skin

■Condition worsens or if symptoms persist for more than 7 days or clear up and occur again within a few days

■Arthritis pain persists for more than 10 days or redness is present, or in conditions affecting children under 12 years of age

If pregnant or breast-feeding:

Ask a health professional before use

Keep out of reach of children:

If swallowed, get medical help or contact a Poison Control Center right away.

Directions

■Adults and children 2 years of age and older: rub a thin ﬁlm over affected area not more than 3 to 4 times daily ■Children under 2 years

of age: consult a physician ■Wash hands after use with cool water

OTHER SAFETY INFORMATION

■Store at 20˚-25˚C (68˚-77˚F)

■Store in a cool dry place away from direct sunlight

Inactive Ingredients

: Aloevera Extract, Arctium Lappa Root (Burdock) Extract, Arnica Montana Flower Extract, Calendula Ofﬁcinalis Extract, Carbopol, FD&C Blue No. 1, FD&C Yellow No. 5, Glycerine, Green Tea Extract, Isopropyl Alcohol, Isopropyl Myristate, Silica, Triethanolamine, Vitamin E, Water